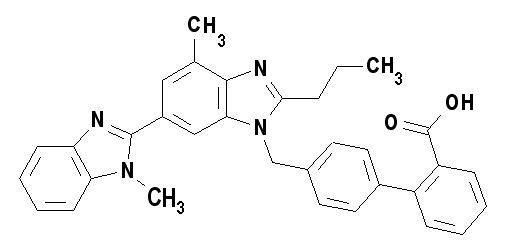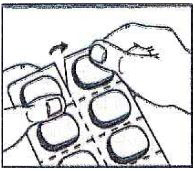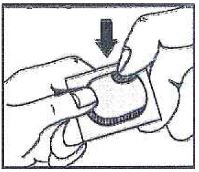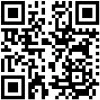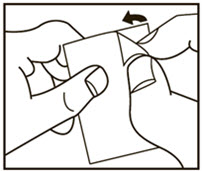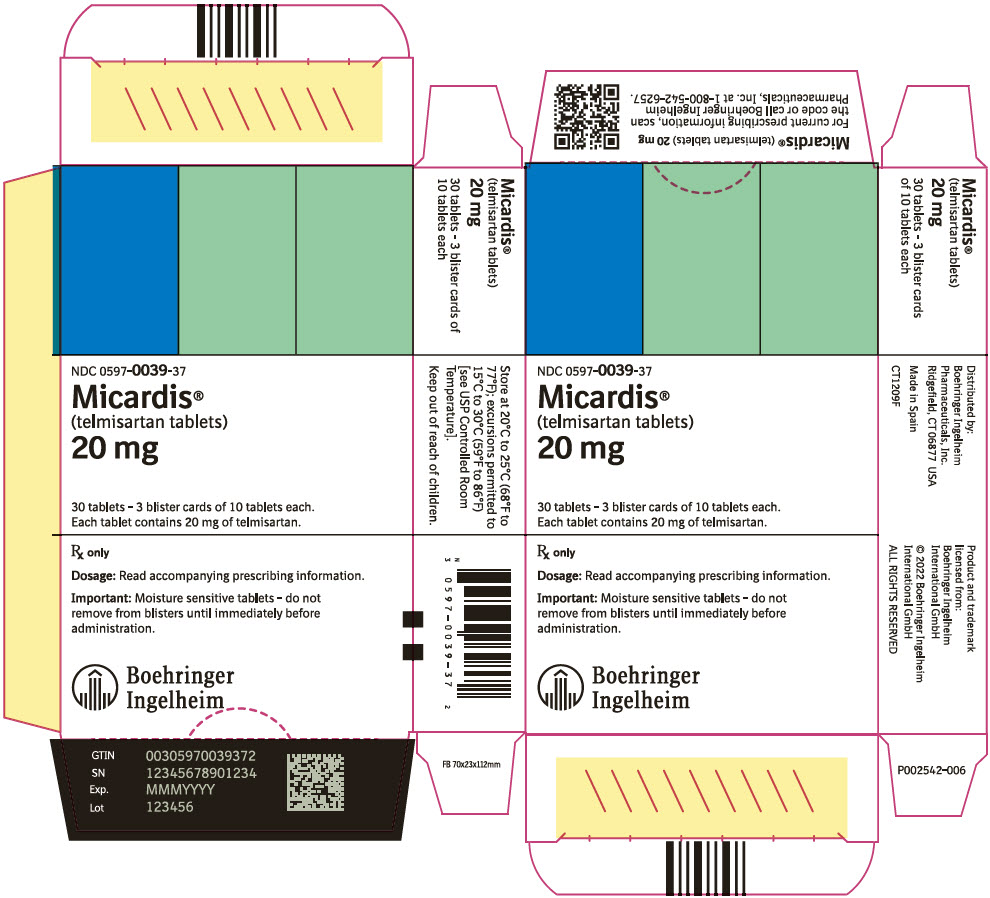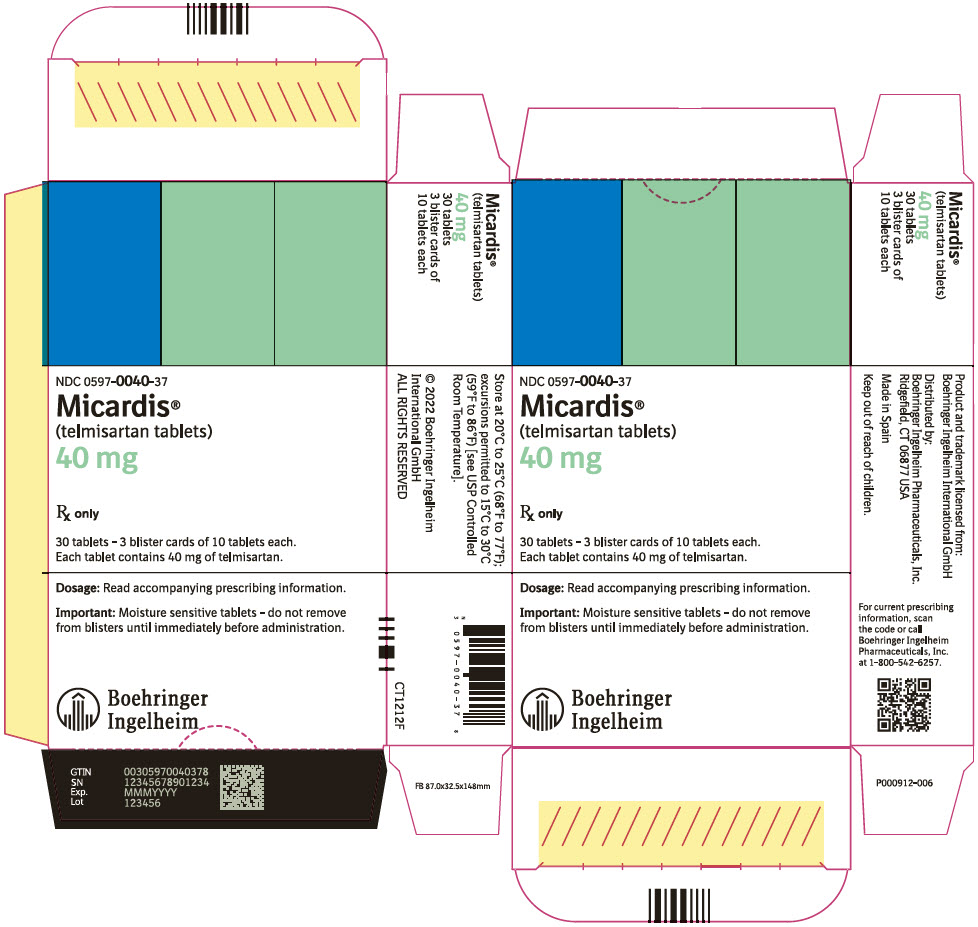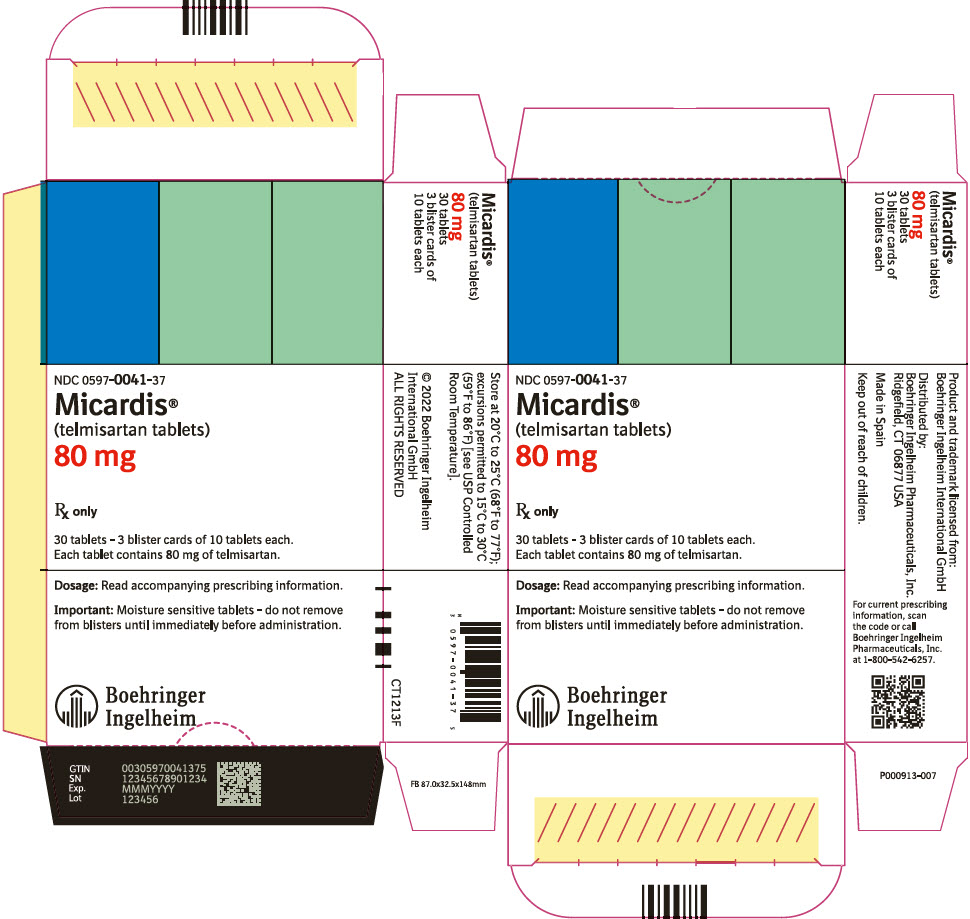 DRUG LABEL: Micardis
NDC: 0597-0039 | Form: TABLET
Manufacturer: Boehringer Ingelheim Pharmaceuticals, Inc.
Category: prescription | Type: HUMAN PRESCRIPTION DRUG LABEL
Date: 20250520

ACTIVE INGREDIENTS: TELMISARTAN 20 mg/1 1

HIGHLIGHTS OF PRESCRIBING INFORMATION

These highlights do not include all the information needed to use MICARDIS safely and effectively. See full prescribing information for MICARDIS.
MICARDIS® (telmisartan tablets), for oral use
Initial U.S. Approval: 1998

WARNING: FETAL TOXICITY

See full prescribing information for complete boxed warning.

- When pregnancy is detected, discontinue MICARDIS as soon as possible (5.1, 8.1)
- Drugs that act directly on the renin-angiotensin system can cause injury and death to the developing fetus (5.1, 8.1)

1 INDICATIONS AND USAGE

MICARDIS is an angiotensin II receptor blocker (ARB) indicated for:

- Treatment of hypertension, to lower blood pressure. Lowering blood pressure reduces the risk of fatal and nonfatal cardiovascular events, primarily strokes and myocardial infarctions. (1.1)
- Cardiovascular (CV) risk reduction in patients unable to take ACE inhibitors (1.2)

2 DOSAGE AND ADMINISTRATION

- May be administered with or without food (2.1)
- When used for cardiovascular risk reduction, monitoring of blood pressure is recommended, and if appropriate, adjustment of medications that lower blood pressure may be necessary (2.2)

Indication | Starting Dose | Dose Range
Hypertension (2.1) | 40 mg once daily | 40 to 80 mg once daily
Cardiovascular Risk Reduction (2.2) | 80 mg once daily | 80 mg once daily

3 DOSAGE FORMS AND STRENGTHS

- Tablets: 20 mg, 40 mg, 80 mg (3)

4 CONTRAINDICATIONS

- Known hypersensitivity (e.g., anaphylaxis or angioedema) to telmisartan or any other component of this product (4)
- Do not co-administer aliskiren with MICARDIS in patients with diabetes (4)

5 WARNINGS AND PRECAUTIONS

- Avoid fetal or neonatal exposure (5.1)
- Hypotension: Correct any volume or salt depletion before initiating therapy. Observe for signs and symptoms of hypotension. (5.2)
- Monitor carefully in patients with impaired hepatic (5.4) or renal function (5.5)
- Avoid concomitant use of an ACE inhibitor and angiotensin receptor blocker (5.6)

6 ADVERSE REACTIONS

- Hypertension: The most common adverse events (≥1%) reported in hypertension trials are back pain, sinusitis, and diarrhea (6.1)
- Cardiovascular risk reduction: The serious adverse events (≥1%) reported in cardiovascular risk reduction trials were intermittent claudication and skin ulcer (6.1)

To report SUSPECTED ADVERSE REACTIONS, contact Boehringer Ingelheim Pharmaceuticals, Inc. at (800) 542-6257 or FDA at 1-800-FDA-1088 or www.fda.gov/medwatch.

7 DRUG INTERACTIONS

- NSAIDs: Increased risk of renal impairment and loss of anti-hypertensive effect (7)
- Do not co-administer aliskiren with MICARDIS in patients with diabetes (7)

8 USE IN SPECIFIC POPULATIONS

- Lactation: Do not breastfeed during treatment with MICARDIS (8.2)
- Geriatric Patients: No overall difference in efficacy or safety vs younger patients, but greater sensitivity of some older individuals cannot be ruled out (8.5)

FULL PRESCRIBING INFORMATION

WARNING: FETAL TOXICITY

- When pregnancy is detected, discontinue MICARDIS as soon as possible [see Warnings and Precautions (5.1) and Use in Specific Populations (8.1)].
- Drugs that act directly on the renin-angiotensin system can cause injury and death to the developing fetus [see Warnings and Precautions (5.1) and Use in Specific Populations (8.1)].

1 INDICATIONS AND USAGE

1.1 Hypertension

MICARDIS is indicated for the treatment of hypertension, to lower blood pressure. Lowering blood pressure reduces the risk of fatal and nonfatal cardiovascular events, primarily strokes and myocardial infarctions. These benefits have been seen in controlled trials of antihypertensive drugs from a wide variety of pharmacologic classes including the class to which this drug principally belongs.

Control of high blood pressure should be part of comprehensive cardiovascular risk management, including, as appropriate, lipid control, diabetes management, antithrombotic therapy, smoking cessation, exercise, and limited sodium intake. Many patients will require more than one drug to achieve blood pressure goals. For specific advice on goals and management, see published guidelines, such as those of the National High Blood Pressure Education Program's Joint National Committee on Prevention, Detection, Evaluation, and Treatment of High Blood Pressure (JNC).

Numerous antihypertensive drugs, from a variety of pharmacologic classes and with different mechanisms of action, have been shown in randomized controlled trials to reduce cardiovascular morbidity and mortality, and it can be concluded that it is blood pressure reduction, and not some other pharmacologic property of the drugs, that is largely responsible for those benefits. The largest and most consistent cardiovascular outcome benefit has been a reduction in the risk of stroke, but reductions in myocardial infarction and cardiovascular mortality also have been seen regularly.

Elevated systolic or diastolic pressure causes increased cardiovascular risk, and the absolute risk increase per mmHg is greater at higher blood pressures, so that even modest reductions of severe hypertension can provide substantial benefit. Relative risk reduction from blood pressure reduction is similar across populations with varying absolute risk, so the absolute benefit is greater in patients who are at higher risk independent of their hypertension (for example, patients with diabetes or hyperlipidemia), and such patients would be expected to benefit from more aggressive treatment to a lower blood pressure goal.

Some antihypertensive drugs have smaller blood pressure effects (as monotherapy) in black patients, and many antihypertensive drugs have additional approved indications and effects (e.g., on angina, heart failure, or diabetic kidney disease). These considerations may guide selection of therapy.

MICARDIS may be used alone or in combination with other antihypertensive agents [see Clinical Studies (14.1)].

1.2 Cardiovascular Risk Reduction

MICARDIS is indicated for reduction of the risk of myocardial infarction, stroke, or death from cardiovascular causes in patients 55 years of age or older at high risk of developing major cardiovascular events who are unable to take ACE inhibitors.

High risk for cardiovascular events can be evidenced by a history of coronary artery disease, peripheral arterial disease, stroke, transient ischemic attack, or high-risk diabetes (insulin-dependent or non-insulin dependent) with evidence of end-organ damage [see Clinical Studies (14.2)]. MICARDIS can be used in addition to other needed treatment (such as antihypertensive, antiplatelet or lipid-lowering therapy) [see Clinical Studies (14.2)].

Studies of telmisartan in this setting do not exclude the possibility that telmisartan may not preserve a meaningful fraction of the effect of the ACE inhibitor to which it was compared. Consider using the ACE inhibitor first, and, if it is stopped for cough only, consider re-trying the ACE inhibitor after the cough resolves.

Use of telmisartan with an ACE inhibitor is not recommended [see Warnings and Precautions (5.6)].

2 DOSAGE AND ADMINISTRATION

2.1 Hypertension

Dosage must be individualized. The usual starting dose of MICARDIS tablets is 40 mg orally once a day. Blood pressure response is dose-related over the range of 20 to 80 mg [see Clinical Studies (14.1)].

Most of the antihypertensive effect is apparent within 2 weeks and maximal reduction is generally attained after 4 weeks.

No initial dosage adjustment is necessary for elderly patients or patients with renal impairment, including those on hemodialysis. Patients on dialysis may develop orthostatic hypotension; their blood pressure should be closely monitored.

MICARDIS tablets may be administered with other antihypertensive agents.

MICARDIS tablets may be administered with or without food.

2.2 Cardiovascular Risk Reduction

The recommended dose of MICARDIS tablets is 80 mg once a day and can be administered with or without food. It is not known whether doses lower than 80 mg of telmisartan are effective in reducing the risk of cardiovascular morbidity and mortality.

When initiating MICARDIS therapy for cardiovascular risk reduction, monitoring of blood pressure is recommended, and if appropriate, adjustment of medications that lower blood pressure may be necessary.

3 DOSAGE FORMS AND STRENGTHS

- 20 mg, white or off-white, round, uncoated tablets imprinted with BI logo on one side and "50H" on the other side
- 40 mg, white or off-white, oblong, uncoated tablets imprinted with BI logo on one side and "51H" on the other side
- 80 mg, white or off-white, oblong, uncoated tablets imprinted with BI logo on one side and "52H" on the other side

4 CONTRAINDICATIONS

MICARDIS is contraindicated in patients with known hypersensitivity (e.g., anaphylaxis or angioedema) to telmisartan or any other component of this product [see Adverse Reactions (6.2)].

Do not co-administer aliskiren with MICARDIS in patients with diabetes [see Drug Interactions (7)].

5 WARNINGS AND PRECAUTIONS

5.1 Fetal Toxicity

Use of drugs that act on the renin-angiotensin system during the second and third trimesters of pregnancy reduces fetal renal function and increases fetal and neonatal morbidity and death. Resulting oligohydramnios can be associated with fetal lung hypoplasia and skeletal deformations. Potential neonatal adverse effects include skull hypoplasia, anuria, hypotension, renal failure, and death. When pregnancy is detected, discontinue MICARDIS as soon as possible [see Use in Specific Populations (8.1)].

5.2 Hypotension

In patients with an activated renin-angiotensin system, such as volume- or salt-depleted patients (e.g., those being treated with high doses of diuretics), symptomatic hypotension may occur after initiation of therapy with MICARDIS. Either correct this condition prior to administration of MICARDIS, or start treatment under close medical supervision with a reduced dose.

If hypotension does occur, the patient should be placed in the supine position and, if necessary, given an intravenous infusion of normal saline. A transient hypotensive response is not a contraindication to further treatment, which usually can be continued without difficulty once the blood pressure has stabilized.

5.3 Hyperkalemia

Hyperkalemia may occur in patients on ARBs, particularly in patients with advanced renal impairment, heart failure, on renal replacement therapy, or on potassium supplements, potassium-sparing diuretics, potassium-containing salt substitutes or other drugs that increase potassium levels. Consider periodic determinations of serum electrolytes to detect possible electrolyte imbalances, particularly in patients at risk.

5.4 Impaired Hepatic Function

As the majority of telmisartan is eliminated by biliary excretion, patients with biliary obstructive disorders or hepatic insufficiency can be expected to have reduced clearance. Initiate telmisartan at low doses and titrate slowly in these patients [see Use in Specific Populations (8.6) and Clinical Pharmacology (12.3)].

5.5 Impaired Renal Function

As a consequence of inhibiting the renin-angiotensin-aldosterone system, anticipate changes in renal function in susceptible individuals. In patients whose renal function may depend on the activity of the renin-angiotensin-aldosterone system (e.g., patients with severe congestive heart failure or renal dysfunction), treatment with angiotensin-converting enzyme (ACE) inhibitors and angiotensin receptor antagonists has been associated with oliguria and/or progressive azotemia and (rarely) with acute renal failure and/or death. Similar results have been reported with MICARDIS [see Clinical Pharmacology (12.3)].

In studies of ACE inhibitors in patients with unilateral or bilateral renal artery stenosis, increases in serum creatinine or blood urea nitrogen were observed. There has been no long-term use of MICARDIS in patients with unilateral or bilateral renal artery stenosis, but anticipate an effect similar to that seen with ACE inhibitors.

5.6 Dual Blockade of the Renin-Angiotensin-Aldosterone System (RAS)

Dual blockade of the RAS with angiotensin-receptor blockers, ACE inhibitors, or aliskiren is associated with increased risks of hypotension, hyperkalemia, and changes in renal function (including acute renal failure) compared to monotherapy.

The ONTARGET trial enrolled 25,620 patients ≥55 years old with atherosclerotic disease or diabetes with end-organ damage, randomizing them to telmisartan only, ramipril only, or the combination, and followed them for a median of 56 months. Patients receiving the combination of MICARDIS and ramipril did not obtain any additional benefit compared to monotherapy, but experienced an increased incidence of renal dysfunction (e.g., acute renal failure) compared with groups receiving telmisartan alone or ramipril alone.

In most patients no benefit has been associated with using two RAS inhibitors concomitantly. In general, avoid combined use of RAS inhibitors. Closely monitor blood pressure, renal function, and electrolytes in patients on MICARDIS and other agents that affect the RAS.

Do not co-administer aliskiren with MICARDIS in patients with diabetes. Avoid concomitant use of aliskiren with MICARDIS in patients with renal impairment (GFR <60 mL/min/1.73 m^2).

6 ADVERSE REACTIONS

The following adverse reaction is described elsewhere in labeling:

- Renal dysfunction upon use with ramipril [see Warnings and Precautions (5.6)]

6.1 Clinical Trials Experience

Because clinical studies are conducted under widely varying conditions, adverse reactions rates observed in the clinical studies of a drug cannot be directly compared to rates in the clinical studies of another drug and may not reflect the rates observed in practice.

Hypertension
MICARDIS has been evaluated for safety in more than 3700 patients, including 1900 treated for over 6 months and more than 1300 for over one year. Adverse experiences have generally been mild and transient in nature and have infrequently required discontinuation of therapy.

In placebo-controlled trials involving 1041 patients treated with various doses of MICARDIS (20 to 160 mg) monotherapy for up to 12 weeks, the overall incidence of adverse events was similar to that in patients treated with placebo.

Adverse events occurring at an incidence of ≥1% in patients treated with MICARDIS and at a greater rate than in patients treated with placebo, irrespective of their causal association, are presented in Table 1.

Table 1 Adverse Events Occurring at an Incidence of ≥1% in Patients Treated with MICARDIS and at a Greater Rate Than Patients Treated with Placebo

 | Telmisartan n=1455 % | Placebo n=380 %
Upper respiratory tract infection | 7 | 6
Back pain | 3 | 1
Sinusitis | 3 | 2
Diarrhea | 3 | 2
Pharyngitis | 1 | 0

In addition to the adverse events in the table, the following events occurred at a rate of ≥1% but were at least as frequent in the placebo group: influenza-like symptoms, dyspepsia, myalgia, urinary tract infection, abdominal pain, headache, dizziness, pain, fatigue, coughing, hypertension, chest pain, nausea, and peripheral edema. Discontinuation of therapy because of adverse events was required in 2.8% of 1455 patients treated with MICARDIS tablets and 6.1% of 380 placebo patients in placebo-controlled clinical trials.

The incidence of adverse events was not dose-related and did not correlate with gender, age, or race of patients.

The incidence of cough occurring with telmisartan in 6 placebo-controlled trials was identical to that noted for placebo-treated patients (1.6%).

In addition to those listed above, adverse events that occurred in more than 0.3% of 3500 patients treated with MICARDIS monotherapy in controlled or open trials are listed below. It cannot be determined whether these events were causally related to MICARDIS tablets:

Autonomic Nervous System: impotence, increased sweating, flushing; Body as a Whole: allergy, fever, leg pain, malaise; Cardiovascular: palpitation, dependent edema, angina pectoris, tachycardia, leg edema, abnormal ECG; CNS: insomnia, somnolence, migraine, vertigo, paresthesia, involuntary muscle contractions, hypoesthesia; Gastrointestinal: flatulence, constipation, gastritis, vomiting, dry mouth, hemorrhoids, gastroenteritis, enteritis, gastroesophageal reflux, toothache, non-specific gastrointestinal disorders; Metabolic: gout, hypercholesterolemia, diabetes mellitus; Musculoskeletal: arthritis, arthralgia, leg cramps; Psychiatric: anxiety, depression, nervousness; Resistance Mechanism: infection, fungal infection, abscess, otitis media; Respiratory: asthma, bronchitis, rhinitis, dyspnea, epistaxis; Skin: dermatitis, rash, eczema, pruritus; Urinary: micturition frequency, cystitis; Vascular: cerebrovascular disorder; and Special Senses: abnormal vision, conjunctivitis, tinnitus, earache.

During initial clinical studies, a single case of angioedema was reported (among a total of 3781 patients treated).

Clinical Laboratory Findings

In placebo-controlled clinical trials, clinically relevant changes in standard laboratory test parameters were rarely associated with administration of MICARDIS tablets.

Hemoglobin: A greater than 2 g/dL decrease in hemoglobin was observed in 0.8% telmisartan patients compared with 0.3% placebo patients. No patients discontinued therapy because of anemia.

Creatinine: A 0.5 mg/dL rise or greater in creatinine was observed in 0.4% telmisartan patients compared with 0.3% placebo patients. One telmisartan-treated patient discontinued therapy because of increases in creatinine and blood urea nitrogen.

Liver Enzymes: Occasional elevations of liver chemistries occurred in patients treated with telmisartan; all marked elevations occurred at a higher frequency with placebo. No telmisartan-treated patients discontinued therapy because of abnormal hepatic function.

Cardiovascular Risk Reduction

Because common adverse reactions were well characterized in studies of telmisartan in hypertension, only adverse events leading to discontinuation and serious adverse events were recorded in subsequent studies of telmisartan for cardiovascular risk reduction. In TRANSCEND (N=5926, 4 years and 8 months of follow-up), discontinuations for adverse events were 8.4% on telmisartan and 7.6% on placebo. The only serious adverse events at least 1% more common on telmisartan than placebo were intermittent claudication (7% vs 6%) and skin ulcer (3% vs 2%).

6.2 Postmarketing Experience

The following adverse reactions have been identified during post-approval use of MICARDIS. Because these reactions are reported voluntarily from a population of uncertain size, it is not always possible to estimate reliably their frequency or establish a causal relationship to drug exposure.

Blood and Lymphatic System Disorders: Anemia, eosinophilia, thrombocytopenia
Gastrointestinal Disorders: Abdominal pain, diarrhea, dyspepsia, nausea
General Disorders and Administration Site Conditions: Asthenia, chest pain, edema, face edema, fatigue, lower limb edema, pain, weakness
Hepato-biliary: Abnormal hepatic function/liver disorder
Immune System Disorders: Anaphylactic reaction, hypersensitivity
Investigations: Increased CPK, uric acid increased
Metabolism and Nutrition Disorders: Hyperkalemia, hypoglycemia (in diabetic patients), hyponatremia
Musculoskeletal and Connective Tissue Disorders: Myalgia
Nervous System Disorders: Dizziness, headache, syncope
Renal and Urinary Disorders: Renal impairment including acute renal failure
Reproductive System and Breast Disorders: Erectile dysfunction
Respiratory, Thoracic and Mediastinal Disorders: Coughing
Skin and Subcutaneous Tissue Disorders: Angioedema (with fatal outcome), angioneurotic edema, drug eruption (toxic skin eruption mostly reported as toxicoderma, rash, and urticaria), erythema, sweating increased, urticaria
Vascular Disorder: Hypotension (including postural hypotension)

Rare cases of rhabdomyolysis have been reported in patients receiving angiotensin II receptor blockers, including MICARDIS.

7 DRUG INTERACTIONS

Aliskiren: Do not co-administer aliskiren with MICARDIS in patients with diabetes. Avoid use of aliskiren with MICARDIS in patients with renal impairment (GFR <60 mL/min).

Digoxin: When MICARDIS was co-administered with digoxin, median increases in digoxin peak plasma concentration (49%) and in trough concentration (20%) were observed. Therefore, monitor digoxin levels when initiating, adjusting, and discontinuing telmisartan for the purpose of keeping the digoxin level within the therapeutic range.

Lithium: Reversible increases in serum lithium concentrations and toxicity have been reported during concomitant administration of lithium with angiotensin II receptor antagonists including MICARDIS. Therefore, monitor serum lithium levels during concomitant use.

Non-Steroidal Anti-Inflammatory Agents including Selective Cyclooxygenase-2 Inhibitors (COX-2 Inhibitors): In patients who are elderly, volume-depleted (including those on diuretic therapy), or with compromised renal function, co-administration of NSAIDs, including selective COX-2 inhibitors, with angiotensin II receptor antagonists, including telmisartan, may result in deterioration of renal function, including possible acute renal failure. These effects are usually reversible. Monitor renal function periodically in patients receiving telmisartan and NSAID therapy.

The antihypertensive effect of angiotensin II receptor antagonists, including telmisartan may be attenuated by NSAIDs including selective COX-2 inhibitors.

8 USE IN SPECIFIC POPULATIONS

8.1 Pregnancy

Risk Summary
MICARDIS can cause fetal harm when administered to a pregnant woman. Use of drugs that act on the renin-angiotensin system during the second and third trimesters of pregnancy reduces fetal renal function and increases fetal and neonatal morbidity and death (see Clinical Considerations). Most epidemiologic studies examining fetal abnormalities after exposure to antihypertensive use in the first trimester have not distinguished drugs affecting the renin-angiotensin system from other antihypertensive agents. Studies in rats and rabbits with telmisartan showed fetotoxicity only at maternally toxic doses (see Data). When pregnancy is detected, discontinue MICARDIS as soon as possible.

The estimated background risk of major birth defects and miscarriage for the indicated population is unknown. All pregnancies have a background risk of birth defect, loss, or other adverse outcomes. In the U.S. general population, the estimated background risk of major birth defects and miscarriage in clinically recognized pregnancies is 2% to 4% and 15% to 20%, respectively.

Clinical Considerations
Disease-associated maternal and/or embryo/fetal risk
Hypertension in pregnancy increases the maternal risk for pre-eclampsia, gestational diabetes, premature delivery, and delivery complications (e.g., need for cesarean section and post-partum hemorrhage). Hypertension increases the fetal risk for intrauterine growth restriction and intrauterine death. Pregnant women with hypertension should be carefully monitored and managed accordingly.

Fetal/Neonatal adverse reactions
Use of drugs that act on the RAS in the second and third trimesters of pregnancy can result in the following: oligohydramnios, reduced fetal renal function leading to anuria and renal failure, fetal lung hypoplasia, skeletal deformations, including skull hypoplasia, hypotension, and death. In the unusual case that there is no appropriate alternative to therapy with drugs affecting the renin-angiotensin system for a particular patient, apprise the mother of the potential risk to the fetus.

In patients taking MICARDIS during pregnancy, perform serial ultrasound examinations to assess the intra-amniotic environment. Fetal testing may be appropriate, based on the week of gestation. If oligohydramnios is observed, discontinue MICARDIS, unless it is considered lifesaving for the mother. Patients and physicians should be aware, however, that oligohydramnios may not appear until after the fetus has sustained irreversible injury.

Closely observe infants with histories of in utero exposure to MICARDIS for hypotension, oliguria, and hyperkalemia. If oliguria or hypotension occurs, support blood pressure and renal perfusion. Exchange transfusions or dialysis may be required as a means of reversing hypotension and/or substituting for disordered renal function [see Use in Specific Populations (8.4)].

Data
Animal Data
No teratogenic effects were observed when telmisartan was administered to pregnant rats at oral doses of up to 50 mg/kg/day and to pregnant rabbits at oral doses up to 45 mg/kg/day. In rabbits, embryolethality associated with maternal toxicity (reduced body weight gain and food consumption) was observed at 45 mg/kg/day [about 12 times the maximum recommended human dose (MRHD) of 80 mg on a mg/m^2 basis]. In rats, maternally toxic (reduction in body weight gain and food consumption) telmisartan doses of 15 mg/kg/day (about 1.9 times the MRHD on a mg/m^2 basis), administered during late gestation and lactation, were observed to produce adverse effects in neonates, including reduced viability, low birth weight, delayed maturation, and decreased weight gain. The no-observed-effect doses for developmental toxicity in rats and rabbits, 5 and 15 mg/kg/day, respectively, are about 0.64 and 3.7 times, on a mg/m^2 basis, the maximum recommended human dose of telmisartan (80 mg/day).

8.2 Lactation

Risk Summary
There is no information regarding the presence of telmisartan in human milk, the effects on the breastfed infant, or the effects on milk production. Telmisartan is present in the milk of lactating rats (see Data). Because of the potential for serious adverse reactions in the breastfed infant including hypotension, hyperkalemia and renal impairment, advise a nursing woman not to breastfeed during treatment with MICARDIS.

Data
Telmisartan was present in the milk of lactating rats at concentrations 1.5 to 2 times those found in plasma from 4 to 8 hours after administration.

8.4 Pediatric Use

Safety and effectiveness in pediatric patients have not been established [see Clinical Pharmacology (12.3)].

Neonates with a history of in utero exposure to MICARDIS
If oliguria or hypotension occurs, support blood pressure and renal perfusion. Exchange transfusions or dialysis may be required as a means of reversing hypotension and/or substituting for disordered renal function.

8.5 Geriatric Use

Of the total number of patients receiving MICARDIS in hypertension clinical studies, 551 (19%) were 65 to 74 years of age and 130 (4%) were 75 years or older. No overall differences in effectiveness and safety were observed in these patients compared to younger patients and other reported clinical experience has not identified differences in responses between the elderly and younger patients, but greater sensitivity of some older individuals cannot be ruled out.

Of the total number of patients receiving MICARDIS in the cardiovascular risk reduction study (ONTARGET), the percentage of patients ≥65 to <75 years of age was 42%; 15% of patients were ≥75 years old. No overall differences in effectiveness and safety were observed in these patients compared to younger patients and other reported clinical experience has not identified differences in responses between the elderly and younger patients, but greater sensitivity of some older individuals cannot be ruled out.

8.6 Hepatic Insufficiency

Monitor carefully and uptitrate slowly in patients with biliary obstructive disorders or hepatic insufficiency [see Warnings and Precautions (5.4)].

10 OVERDOSAGE

Limited data are available with regard to overdosage in humans. The most likely manifestation of overdosage with MICARDIS tablets would be hypotension, dizziness and tachycardia; bradycardia could occur from parasympathetic (vagal) stimulation. If symptomatic hypotension should occur, supportive treatment should be instituted. Telmisartan is not removed by hemofiltration and is not dialyzable.

11 DESCRIPTION

MICARDIS is a non-peptide angiotensin II receptor (type AT1) antagonist.

Telmisartan is chemically described as 4'-[(1,4'-dimethyl-2'-propyl [2,6'-bi-1H-benzimidazol]-1'-yl)methyl]-[1,1'-biphenyl]-2-carboxylic acid. Its empirical formula is C33H30N4O2, its molecular weight is 514.63, and its structural formula is:

Telmisartan is a white to slightly yellowish solid. It is practically insoluble in water and in the pH range of 3 to 9, sparingly soluble in strong acid (except insoluble in hydrochloric acid), and soluble in strong base.

MICARDIS is available as tablets for oral administration, containing 20 mg, 40 mg or 80 mg of telmisartan. The tablets contain the following inactive ingredients: sodium hydroxide, meglumine, povidone, sorbitol, and magnesium stearate. MICARDIS tablets are hygroscopic and require protection from moisture.

12 CLINICAL PHARMACOLOGY

12.1 Mechanism of Action

Angiotensin II is formed from angiotensin I in a reaction catalyzed by angiotensin-converting enzyme (ACE, kininase II). Angiotensin II is the principal pressor agent of the renin-angiotensin system, with effects that include vasoconstriction, stimulation of synthesis and release of aldosterone, cardiac stimulation, and renal reabsorption of sodium. Telmisartan blocks the vasoconstrictor and aldosterone-secreting effects of angiotensin II by selectively blocking the binding of angiotensin II to the AT1 receptor in many tissues, such as vascular smooth muscle and the adrenal gland. Its action is therefore independent of the pathways for angiotensin II synthesis.

There is also an AT2 receptor found in many tissues, but AT2 is not known to be associated with cardiovascular homeostasis. Telmisartan has much greater affinity (>3,000 fold) for the AT1 receptor than for the AT2 receptor.

Blockade of the renin-angiotensin system with ACE inhibitors, which inhibit the biosynthesis of angiotensin II from angiotensin I, is widely used in the treatment of hypertension. ACE inhibitors also inhibit the degradation of bradykinin, a reaction also catalyzed by ACE. Because telmisartan does not inhibit ACE (kininase II), it does not affect the response to bradykinin. Whether this difference has clinical relevance is not yet known. Telmisartan does not bind to or block other hormone receptors or ion channels known to be important in cardiovascular regulation.

Blockade of the angiotensin II receptor inhibits the negative regulatory feedback of angiotensin II on renin secretion, but the resulting increased plasma renin activity and angiotensin II circulating levels do not overcome the effect of telmisartan on blood pressure.

12.2 Pharmacodynamics

In normal volunteers, a dose of telmisartan 80 mg inhibited the pressor response to an intravenous infusion of angiotensin II by about 90% at peak plasma concentrations with approximately 40% inhibition persisting for 24 hours.

Plasma concentration of angiotensin II and plasma renin activity (PRA) increased in a dose-dependent manner after single administration of telmisartan to healthy subjects and repeated administration to hypertensive patients. The once-daily administration of up to 80 mg telmisartan to healthy subjects did not influence plasma aldosterone concentrations. In multiple dose studies with hypertensive patients, there were no clinically significant changes in electrolytes (serum potassium or sodium), or in metabolic function (including serum levels of cholesterol, triglycerides, HDL, LDL, glucose, or uric acid).

In 30 hypertensive patients with normal renal function treated for 8 weeks with telmisartan 80 mg or telmisartan 80 mg in combination with hydrochlorothiazide 12.5 mg, there were no clinically significant changes from baseline in renal blood flow, glomerular filtration rate, filtration fraction, renovascular resistance, or creatinine clearance.

12.3 Pharmacokinetics

Absorption:
Following oral administration, peak concentrations (Cmax) of telmisartan are reached in 0.5 to 1 hour after dosing. Food slightly reduces the bioavailability of telmisartan, with a reduction in the area under the plasma concentration-time curve (AUC) of about 6% with the 40 mg tablet and about 20% after a 160 mg dose. The absolute bioavailability of telmisartan is dose dependent. At 40 mg and 160 mg, the bioavailability was 42% and 58%, respectively. The pharmacokinetics of orally administered telmisartan are nonlinear over the dose range 20 mg to 160 mg, with greater than proportional increases of plasma concentrations (Cmax and AUC) with increasing doses. Telmisartan shows bi-exponential decay kinetics with a terminal elimination half-life of approximately 24 hours. Trough plasma concentrations of telmisartan with once daily dosing are about 10% to 25% of peak plasma concentrations. Telmisartan has an accumulation index in plasma of 1.5 to 2.0 upon repeated once daily dosing.

Distribution
Telmisartan is highly bound to plasma proteins (>99.5%), mainly albumin and α1 - acid glycoprotein. Plasma protein binding is constant over the concentration range achieved with recommended doses. The volume of distribution for telmisartan is approximately 500 liters indicating additional tissue binding.

Metabolism and Elimination
Following either intravenous or oral administration of ^14C-labeled telmisartan, most of the administered dose (>97%) was eliminated unchanged in feces via biliary excretion; only minute amounts were found in the urine (0.91% and 0.49% of total radioactivity, respectively).

Telmisartan is metabolized by conjugation to form a pharmacologically inactive acyl glucuronide; the glucuronide of the parent compound is the only metabolite that has been identified in human plasma and urine. After a single dose, the glucuronide represents approximately 11% of the measured radioactivity in plasma. The cytochrome P450 isoenzymes are not involved in the metabolism of telmisartan.

Total plasma clearance of telmisartan is >800 mL/min. Terminal half-life and total clearance appear to be independent of dose.

Specific Populations
Renal Insufficiency
No dosage adjustment is necessary in patients with decreased renal function. Telmisartan is not removed from blood by hemofiltration and is not dialyzable [see Warnings and Precautions (5.5) and Dosage and Administration (2.1)].
Hepatic Insufficiency
In patients with hepatic insufficiency, plasma concentrations of telmisartan are increased, and absolute bioavailability approaches 100% [see Warnings and Precautions (5.4) and Use in Specific Populations (8.6)].
Gender
Plasma concentrations of telmisartan are generally 2 to 3 times higher in females than in males. In clinical trials, however, no significant increases in blood pressure response or in the incidence of orthostatic hypotension were found in women. No dosage adjustment is necessary.
Geriatric Patients
The pharmacokinetics of telmisartan do not differ between the elderly and those younger than 65 years [see Dosage and Administration (2.1)].
Pediatric Patients
Telmisartan pharmacokinetics have not been investigated in patients <18 years of age.

Drug Interaction Studies
Telmisartan
Ramipril and Ramiprilat: Co-administration of telmisartan 80 mg once daily and ramipril 10 mg once daily to healthy subjects increases steady-state Cmax and AUC of ramipril 2.3- and 2.1-fold, respectively, and Cmax and AUC of ramiprilat 2.4- and 1.5-fold, respectively. In contrast, Cmax and AUC of telmisartan decrease by 31% and 16%, respectively. When co-administering telmisartan and ramipril, the response may be greater because of the possibly additive pharmacodynamic effects of the combined drugs, and also because of the increased exposure to ramipril and ramiprilat in the presence of telmisartan.

Other Drugs: Co-administration of telmisartan did not result in a clinically significant interaction with acetaminophen, amlodipine, glyburide, simvastatin, hydrochlorothiazide, warfarin, or ibuprofen. Telmisartan is not metabolized by the cytochrome P450 system and had no effects in vitro on cytochrome P450 enzymes, except for some inhibition of CYP2C19. Telmisartan is not expected to interact with drugs that inhibit cytochrome P450 enzymes; it is also not expected to interact with drugs metabolized by cytochrome P450 enzymes, except for possible inhibition of the metabolism of drugs metabolized by CYP2C19.

13 NONCLINICAL TOXICOLOGY

13.1 Carcinogenesis, Mutagenesis, Impairment of Fertility

There was no evidence of carcinogenicity when telmisartan was administered in the diet to mice and rats for up to 2 years. The highest doses administered to mice (1000 mg/kg/day) and rats (100 mg/kg/day) are, on a mg/m^2 basis, about 59 and 13 times, respectively, the maximum recommended human dose (MRHD) of telmisartan. These same doses have been shown to provide average systemic exposures to telmisartan >100 times and >25 times, respectively, the systemic exposure in humans receiving the MRHD (80 mg/day).

Genotoxicity assays did not reveal any telmisartan-related effects at either the gene or chromosome level. These assays included bacterial mutagenicity tests with Salmonella and E. coli (Ames), a gene mutation test with Chinese hamster V79 cells, a cytogenetic test with human lymphocytes, and a mouse micronucleus test.

No drug-related effects on the reproductive performance of male and female rats were noted at 100 mg/kg/day (the highest dose administered), about 13 times, on a mg/m^2 basis, the MRHD of telmisartan. This dose in the rat resulted in an average systemic exposure (telmisartan AUC as determined on day 6 of pregnancy) at least 50 times the average systemic exposure in humans at the MRHD (80 mg/day).

14 CLINICAL STUDIES

14.1 Hypertension

The antihypertensive effects of MICARDIS have been demonstrated in six principal placebo-controlled clinical trials, studying a range of 20 to 160 mg; one of these examined the antihypertensive effects of telmisartan and hydrochlorothiazide in combination. The studies involved a total of 1773 patients with mild to moderate hypertension (diastolic blood pressure of 95 to 114 mmHg), 1031 of whom were treated with telmisartan. Following once daily administration of telmisartan, the magnitude of blood pressure reduction from baseline after placebo subtraction was approximately (SBP/DBP) 6-8/6 mmHg for 20 mg, 9-13/6-8 mmHg for 40 mg, and 12-13/7-8 mmHg for 80 mg. Larger doses (up to 160 mg) did not appear to cause a further decrease in blood pressure.

Upon initiation of antihypertensive treatment with telmisartan, blood pressure was reduced after the first dose, with a maximal reduction by about 4 weeks. With cessation of treatment with MICARDIS tablets, blood pressure gradually returned to baseline values over a period of several days to one week. During long-term studies (without placebo control) the effect of telmisartan appeared to be maintained for up to at least one year. The antihypertensive effect of telmisartan is not influenced by patient age, gender, weight, or body mass index. Blood pressure response in black patients (usually a low-renin population) is noticeably less than that in Caucasian patients. This has been true for most, but not all, angiotensin II antagonists and ACE inhibitors.

In a controlled study, the addition of telmisartan to hydrochlorothiazide produced an additional dose-related reduction in blood pressure that was similar in magnitude to the reduction achieved with telmisartan monotherapy. Hydrochlorothiazide also had an added blood pressure effect when added to telmisartan.

The onset of antihypertensive activity occurs within 3 hours after administration of a single oral dose. At doses of 20, 40, and 80 mg, the antihypertensive effect of once daily administration of telmisartan is maintained for the full 24-hour dose interval. With automated ambulatory blood pressure monitoring and conventional blood pressure measurements, the 24-hour trough-to-peak ratio for 40 to 80 mg doses of telmisartan was 70% to 100% for both systolic and diastolic blood pressure. The incidence of symptomatic orthostasis after the first dose in all controlled trials was low (0.04%).

There were no changes in the heart rate of patients treated with telmisartan in controlled trials.

There are no trials of MICARDIS demonstrating reductions in cardiovascular risk in patients with hypertension, but at least one pharmacologically similar drug has demonstrated such benefits.

14.2 Cardiovascular Risk Reduction

Support for use to reduce the risk of cardiovascular events was obtained in a pair of studies. Both enrolled subjects age ≥55 years, at high cardiovascular risk as evidenced by coronary artery disease (75%), diabetes mellitus (27%) accompanied with end-organ damage (e.g., retinopathy, left ventricular hypertrophy, and, in ONTARGET only, macro- or microalbuminuria), stroke (16%), peripheral vascular disease (13%), or transient ischemic attack (4%). Patients without a history of intolerance to ACE inhibitors entered ONTARGET, and those with such a history, usually cough (90%), entered TRANSCEND, but patients with >1+ proteinuria on dipstick were excluded from TRANSCEND. For both ONTARGET and TRANSCEND trials, the primary 4-component composite endpoint was death from cardiovascular causes, myocardial infarction, stroke, and hospitalization for heart failure. The secondary 3-component composite endpoint was death from cardiovascular causes, myocardial infarction, and stroke.

ONTARGET was a randomized, active-controlled, multinational, double-blind study in 25,620 patients who were randomized to telmisartan 80 mg, ramipril 10 mg, or their combination. The population studied was 73% male, 74% Caucasian, 14% Asian, and 57% were 65 years of age or older. Baseline therapy included acetylsalicylic acid (76%), lipid lowering agents (64%), beta-blockers (57%), calcium channel blockers (34%), nitrates (29%), and diuretics (28%). Mean blood pressure at randomization was 134/77 mmHg. The mean duration of follow up was about 4 years and 6 months. During the study, 22.0% (n=1878) of telmisartan patients discontinued the active treatment, compared to 24.4% (n=2095) of ramipril patients and 25.3% (n=2152) of telmisartan/ramipril patients.

TRANSCEND randomized patients to telmisartan 80 mg (n=2954) or placebo (n=2972). The mean duration of follow up was 4 years and 8 months. The population studied was 57% male, 62% Caucasian, 21% Asian, and 60% were 65 years of age or older. Baseline therapy included acetylsalicylic acid (75%), lipid lowering agents (58%), beta-blockers (58%), calcium channel blockers (41%), nitrates (34%) and diuretics (33%). Mean blood pressure at randomization was 135/78 mmHg. During the study, 17.7% (n=523) of telmisartan patients discontinued the active treatment, compared to 19.4% (n=576) of placebo patients.

The results for the TRANSCEND trial are summarized in Table 2, and the results for ONTARGET are summarized in Table 3, below:

Table 2 Incidence of the Primary and Secondary Outcomes from TRANSCEND
 | Telmisartan vs. Placebo (n=2954) (n=2972)
 | No. of Events Telmisartan / Placebo | Hazard Ratio 95% CI | p-value
*Composite of CV death, myocardial infarction, stroke, or hospitalization for heart failure | 465 (15.7%) / 504 (17.0%) | 0.92 (0.81 – 1.05) | 0.2129
*Composite of CV death, myocardial infarction, or stroke | 384 (13.0%) / 440 (14.8%) | 0.87 (0.76 – 1.00) | 0.0483
Individual components of the primary composite endpoint | No. of Events Telmisartan / Placebo | Hazard Ratio 95% CI | p-value
**All non-fatal MI | 114 (3.9%) / 145 (4.9%) | 0.79 (0.62 – 1.01) | 0.0574
**All non-fatal strokes | 112 (3.8%) / 136 (4.6%) | 0.83 (0.64 – 1.06) | 0.1365
*The primary endpoint was defined as the time to first event. In case of multiple simultaneous events, all individual events were considered; the sum of patients with individual outcomes may exceed the number of patients with composite (primary or secondary) outcomes.
**For individual components of the primary composite endpoints, all events, regardless whether or not they were the first event, were considered. Therefore, they are more than the first events considered for the primary or secondary composite endpoint.

Table 3 Incidence of the Primary and Secondary Outcomes from ONTARGET
 | Telmisartan vs. Ramipril (n=8542) (n=8576)
 | No. of Events Telmisartan / Ramipril | Hazard Ratio 97.5% CI
Composite of CV death, myocardial infarction, stroke, or hospitalization for heart failure | 1423 (16.7%) / 1412 (16.5%) | 1.01 (0.93 – 1.10)
Composite of CV death, myocardial infarction, or stroke | 1190 (13.9%) / 1210 (14.1%) | 0.99 (0.90 – 1.08)

Although the event rates in ONTARGET were similar on telmisartan and ramipril, the results did not unequivocally rule out that MICARDIS may not preserve a meaningful fraction of the effect of ramipril in reducing cardiovascular events. However, the results of both ONTARGET and TRANSCEND do adequately support MICARDIS being more effective than placebo would be in this setting, particularly for the endpoint of time to cardiovascular death, myocardial infarction, or stroke.

In ONTARGET, there was no evidence that combining ramipril and MICARDIS reduced the risk of death from cardiovascular causes, myocardial infarction, stroke, or hospitalization for heart failure greater than ramipril alone; instead, patients who received the combination of ramipril and telmisartan in ONTARGET experienced an increased incidence of clinically important renal dysfunction (e.g., acute renal failure) compared to patients receiving MICARDIS or ramipril alone.

Multiple sub-group analyses did not demonstrate any differences in the 4-component composite primary endpoint based on age, gender, or ethnicity for either ONTARGET or TRANSCEND trial.

16 HOW SUPPLIED/STORAGE AND HANDLING

MICARDIS is available as white or off-white, uncoated tablets containing telmisartan 20 mg, 40 mg, or 80 mg. Tablets are marked with the Boehringer Ingelheim company symbol on one side, and on the other side, with either "50H", "51H", or "52H" for the 20 mg, 40 mg, and 80 mg strengths, respectively. Tablets are provided as follows:

MICARDIS tablets 20 mg are round and individually blister-sealed in cartons of 30 tablets as 3 x 10 cards (NDC 0597-0039-37).

MICARDIS tablets 40 mg are oblong shaped and individually blister-sealed in cartons of 30 tablets as 3 x 10 cards (NDC 0597-0040-37).

MICARDIS tablets 80 mg are oblong shaped and individually blister-sealed in cartons of 30 tablets as 3 x 10 cards (NDC 0597-0041-37).

Storage
Store at 20°C to 25°C (68°F to 77°F); excursions permitted to 15°C to 30°C (59°F to 86°F) [see USP Controlled Room Temperature]. Tablets should not be removed from blisters until immediately before administration.

17 PATIENT COUNSELING INFORMATION

Advise the patient to read the FDA-approved patient labeling (Patient Information)

Pregnancy
Advise female patients of childbearing age about the consequences of exposure to MICARDIS during pregnancy. Discuss treatment options with women planning to become pregnant. Tell patients to report pregnancies to their physicians as soon as possible [see Warnings and Precautions (5.1) and Use in Specific Populations (8.1)].

Lactation
Advise nursing women not to breastfeed during treatment with MICARDIS [see Use in Specific Populations (8.2)].

Symptomatic Hypotension and Syncope
Advise patients that lightheadedness can occur, especially during the first days of therapy, and to report it to their healthcare provider. Inform patients that inadequate fluid intake, excessive perspiration, diarrhea, or vomiting can lead to an excessive fall in blood pressure, with the same consequences of lightheadedness and possible syncope. Advise patients to contact their healthcare provider if syncope occurs [see Warnings and Precautions (5.2)].

Potassium Supplements
Advise patients not to use potassium supplements or salt substitutes that contain potassium without consulting the prescribing healthcare provider [see Warnings and Precautions (5.3)].

Distributed by:
Boehringer Ingelheim Pharmaceuticals, Inc.
Ridgefield, CT 06877 USA

Licensed from:
Boehringer Ingelheim International GmbH, Ingelheim, Germany

Copyright © 2022 Boehringer Ingelheim International GmbH
ALL RIGHTS RESERVED

MICARDIS® is a registered trademark of and used under license from Boehringer Ingelheim International GmbH.

Boehringer Ingelheim Pharmaceuticals, Inc. either owns or uses the ONTARGET® and TRANSCEND™ trademarks under license.

The other brands listed are trademarks of their respective owners and are not trademarks of Boehringer Ingelheim Pharmaceuticals, Inc.

COL10714AL272022
SPL10716A

Patient Information

MICARDIS® (my-CAR-dis)
(telmisartan tablets)

Read this Patient Information before you start taking MICARDIS tablets and each time you get a refill. There may be new information. This information does not take the place of talking to your doctor about your medical condition or your treatment.

What is the most important information I should know about MICARDIS tablets?

MICARDIS can cause harm or death to an unborn baby. Talk to your doctor about other ways to lower your blood pressure if you plan to become pregnant. If you get pregnant while taking MICARDIS, tell your doctor right away.

What is MICARDIS?

MICARDIS is a prescription medicine used:

- to treat high blood pressure (hypertension)
- in certain high risk people aged 55 years and older to help lower their risk of having certain cardiovascular problems such as stroke, heart attack, or death

It is not known if MICARDIS is safe and effective in children.

Who should not take MICARDIS?

You should not take MICARDIS tablets if you are allergic (hypersensitive) to the active ingredient (telmisartan) or any of the other ingredients listed at the end of this leaflet.

For patients with diabetes, if you are taking MICARDIS you should not take aliskiren.

What should I tell my doctor before taking MICARDIS tablets?

Before you take MICARDIS tablets, tell your doctor if you:

- are pregnant or are planning to become pregnant. See "What is the most important information I should know about MICARDIS tablets?"
- are breast-feeding or plan to breast-feed. It is not known if MICARDIS passes into your breast milk. You and your doctor should decide if you will take MICARDIS tablets or breast-feed. You should not do both. Talk with your doctor about the best way to feed your baby if you take MICARDIS tablets.
- have liver problems
- have kidney problems
- have heart problems
- have any other medical conditions

Tell your doctor about all the medicines you take, including prescription and non-prescription medicines, vitamins, and herbal supplements.

For patients with diabetes, if you are taking MICARDIS you should not take aliskiren.

MICARDIS may affect the way other medicines work, and other medicines may affect how MICARDIS works. Especially tell your doctor if you take:

- aliskiren
- digoxin (Lanoxin®)
- lithium (Lithobid®, lithium carbonate, lithium citrate)
- aspirin or other non-steroidal anti-inflammatory drugs (NSAIDs)
- other medicines used to treat your high blood pressure or heart problem
- water pills (diuretic)

Know the medicines you take. Keep a list of them and show it to your doctor or pharmacist when you get a new medicine.

How should I take MICARDIS tablets?

- Take MICARDIS tablets exactly as your doctor tells you to take it.
- Your doctor will tell you how much MICARDIS to take and when to take it.
- Do not change your dose unless your doctor tells you to.
- Take MICARDIS one time each day at the same time.
- Take MICARDIS tablets with or without food.
- If you miss a dose, take it as soon as you remember. If it is close to your next dose, do not take the missed dose. Take the next dose at your regular time.
- If you take too much MICARDIS, call your doctor, or go to the nearest hospital emergency room right away.
- Read the "How to Open the Blister" at the end of this leaflet before you use MICARDIS. Talk with your doctor if you do not understand the instructions.

What are the possible side effects of MICARDIS tablets?

MICARDIS tablets may cause serious side effects, including:

- Injury or death to your unborn baby. See "What is the most important information I should know about MICARDIS tablets?"
- Low blood pressure (hypotension) is most likely to happen if you also:
  - take water pills (diuretics)
  - are on a low-salt diet
  - get dialysis treatments
  - have heart problems
  - get sick with vomiting or diarrhea

If you feel faint or dizzy, lie down and call your doctor right away.

- Kidney problems, which may get worse if you already have kidney disease. You may have changes in your kidney test results, and you may need a lower dose of MICARDIS tablets. Call your doctor if you get:
  - swelling in your feet, ankles, or hands
  - unexplained weight gain

Call your doctor right away if you get any of the symptoms listed above.

- High potassium in the blood (hyperkalemia). Your doctor may check your potassium levels as needed.

Rare, serious allergic reactions may happen. Tell your doctor right away if you get any of these symptoms:

- swelling of the face, tongue, throat
- difficulty breathing
- skin rash

The most common side effects of MICARDIS tablets include:

- sinus pain and congestion (sinusitis)
- back pain
- diarrhea

These are not all the possible side effects with MICARDIS tablets. Tell your doctor if you have any side effect that bothers you or that does not go away.

Call your doctor for medical advice about side effects. You may report side effects to FDA at 1-800-FDA-1088.

How should I store MICARDIS tablets?

- Store MICARDIS tablets at room temperature between 68°F to 77°F (20°C to 25°C).
- Do not remove MICARDIS tablets from blisters until right before you take them.

Keep MICARDIS tablets and all medicines out of the reach of children.

General information about MICARDIS tablets

Medicines are sometimes prescribed for purposes other than those listed in a Patient Information leaflet. Do not use MICARDIS tablets for a condition for which it was not prescribed. Do not give MICARDIS tablets to other people, even if they have the same condition you have. It may harm them.

This Patient Information leaflet summarizes the most important information about MICARDIS tablets. If you would like more information, talk with your doctor. You can ask your pharmacist or doctor for information about MICARDIS tablets that is written for health professionals.

For current prescribing information, scan the code or call Boehringer Ingelheim Pharmaceuticals, Inc. at 1-800-542-6257.

What are the ingredients in MICARDIS tablets?

Active Ingredient: telmisartan

Inactive Ingredients: sodium hydroxide, meglumine, povidone, sorbitol, and magnesium stearate

What is High Blood Pressure (Hypertension)?

Blood pressure is the force in your blood vessels when your heart beats and when your heart rests. You have high blood pressure when the force is too much. MICARDIS tablets can help your blood vessels relax so your blood pressure is lower. Medicines that lower your blood pressure lower your chance of having a stroke or heart attack.

High blood pressure makes the heart work harder to pump blood throughout the body and causes damage to the blood vessels. If high blood pressure is not treated, it can lead to stroke, heart attack, heart failure, kidney failure, and vision problems.

What is Cardiovascular Risk?

Patients older than 55 years of age who have been diagnosed with blood vessel disease in the heart, legs, or brain (coronary, peripheral, or cerebral vascular disease) or diabetes with end organ damage (for example: kidney, heart, and brain) are at higher risk of cardiovascular events (for example: death from cardiovascular causes, stroke, and/or heart attack).

How to open the blister:

1. Tear (You may also use scissors to tear the blister apart)

2. Peel (Peel off the paper layer from the aluminum foil)

3. Push (Push the tablet through the aluminum foil)

This Patient Information has been approved by the U.S. Food and Drug Administration

Distributed by:
Boehringer Ingelheim Pharmaceuticals, Inc.
Ridgefield, CT 06877 USA

Licensed from:
Boehringer Ingelheim International GmbH, Ingelheim, Germany

Copyright © 2022 Boehringer Ingelheim International GmbH
ALL RIGHTS RESERVED

MICARDIS® is a registered trademark of and used under license from Boehringer Ingelheim International GmbH.

Boehringer Ingelheim Pharmaceuticals, Inc. either owns or uses the ONTARGET® and TRANSCEND™ trademarks under license.

The other brands listed are trademarks of their respective owners and are not trademarks of Boehringer Ingelheim Pharmaceuticals, Inc.

Revised: December 2022

COL10714AL272022
SPL10716A

PRINCIPAL DISPLAY PANEL - 20 mg Tablet Blister Pack Carton

NDC 0597-0039-37
Micardis®
(telmisartan tablets)
20 mg

30 tablets - 3 blister cards of 10 tablets each.
Each tablet contains 20 mg of telmisartan.

Rx only

Dosage: Read accompanying prescribing information.

Important: Moisture sensitive tablets - do not
remove from blisters until immediately before
administration.

Boehringer
Ingelheim

PRINCIPAL DISPLAY PANEL - 40 mg Tablet Blister Pack Carton

NDC 0597-0040-37
Micardis®
(telmisartan tablets)
40 mg

Rx only

30 tablets - 3 blister cards of 10 tablets each.
Each tablet contains 40 mg of telmisartan.

Dosage: Read accompanying prescribing information.

Important: Moisture sensitive tablets - do not remove
from blisters until immediately before administration.

Boehringer
Ingelheim

PRINCIPAL DISPLAY PANEL - 80 mg Tablet Blister Pack Carton

NDC 0597-0041-37
Micardis®
(telmisartan tablets)
80 mg

Rx only

30 tablets - 3 blister cards of 10 tablets each.
Each tablet contains 80 mg of telmisartan.

Dosage: Read accompanying prescribing information.

Important: Moisture sensitive tablets - do not remove
from blisters until immediately before administration.

Boehringer
Ingelheim